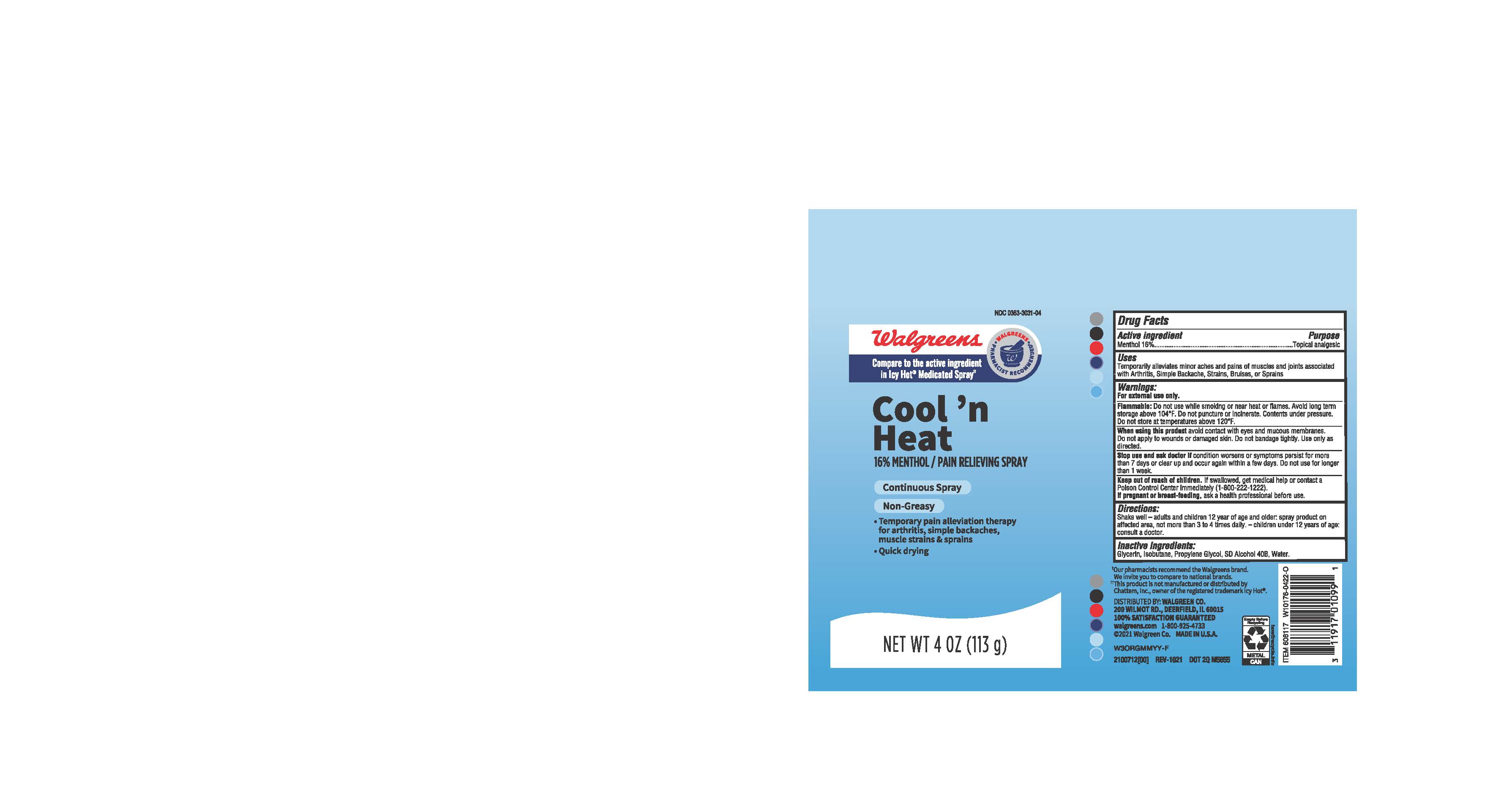 DRUG LABEL: Walgreens Cool and Heat
NDC: 0363-3031 | Form: AEROSOL, SPRAY
Manufacturer: Walgreens
Category: otc | Type: HUMAN OTC DRUG LABEL
Date: 20241211

ACTIVE INGREDIENTS: MENTHOL 16 g/100 g
INACTIVE INGREDIENTS: DEHYDRATED ALCOHOL; PROPYLENE GLYCOL; GLYCERIN; WATER; ISOBUTANE

Walgreens Cool and Heat Menthol Spray

ACTIVE INGREDIENT

Menthol 16%

PURPOSE

Topical analgesic

INDICATIONS AND USAGE

Temporarily alleviates minor aches and pains of muscles and joints associated with Arthritis, Simple Backache, Strains, Bruises, or Sprains

WARNINGS

For external use only.

Flammable: Do not use while smoking or near heat or flames. Avoid long term storage above 104°F. Do not puncture or incinerate. Contents under pressure. Do not store at temperatures above 120°F.

WHEN USING

Avoid contact with eyes and mucous membranes.

Do not apply to wounds or damaged skin. Do not bondage tightly. Use only as directed.

Stop use and ask doctor if condition worsens or symptoms persist for more than 7 days or clear up and occur again within a few days. Do not use for longer than 1 week.

KEEP OUT OF REACH OF CHILDREN

If swallowed, get medical help or contact a Poison Control Center immediately (1-800-222-1222).

If pregnant or breast- feeding, ask a health professional before use.

DOSAGE AND ADMINISTRATION

Shake well- adult and children 12 year of age and older: spray product on affected area, not more than 3 to 4 times daily.

Children under 12 years of age: consult a doctor.

INACTIVE INGREDIENT

Glycerin, Isobutane, Propylene Glycol, SD Alcohol 40B, Water.